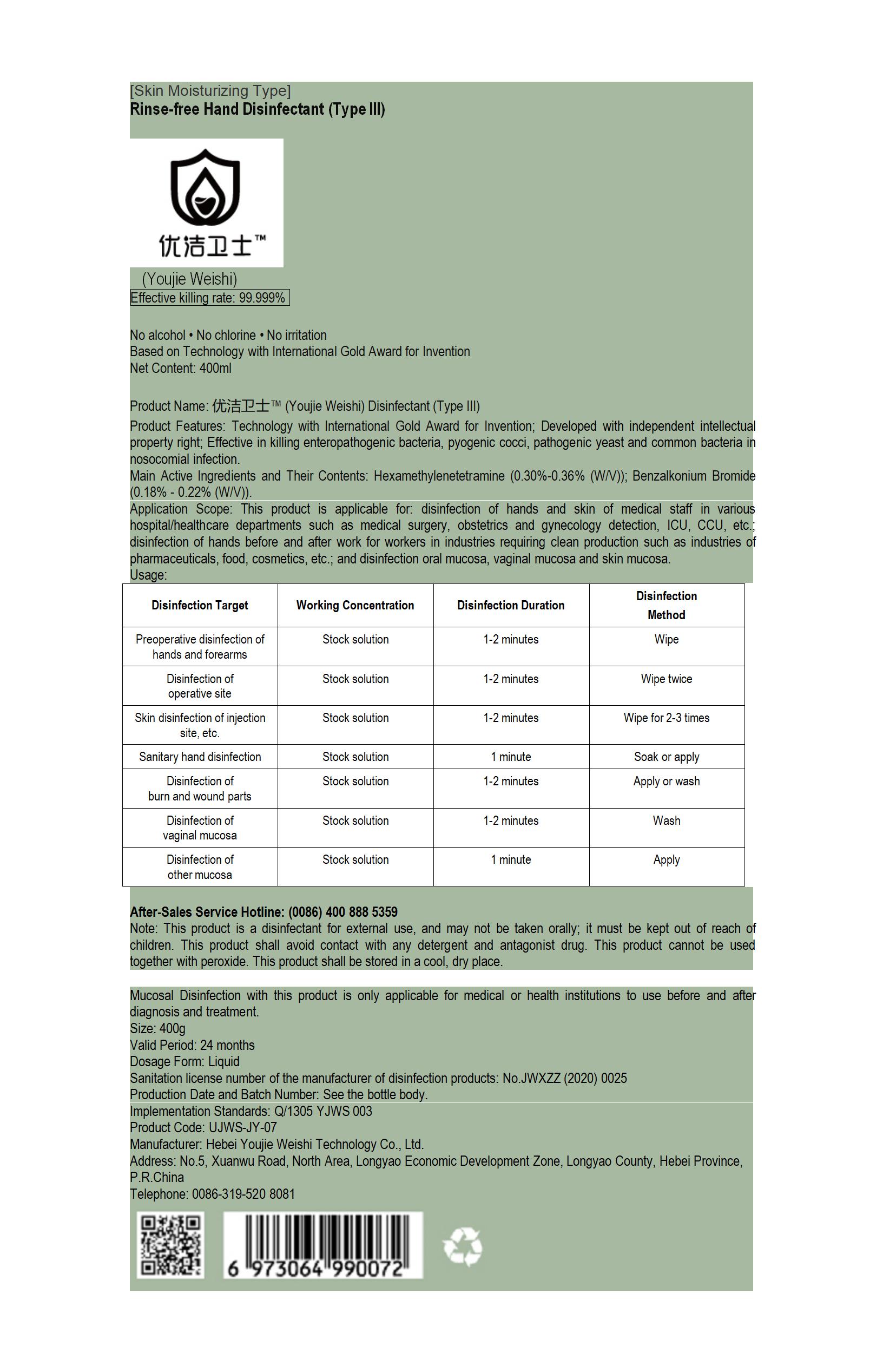 DRUG LABEL: Youjie Weishi Rinse-free Hand Disinfectant
NDC: 55455-009 | Form: LIQUID
Manufacturer: Hebei Youjie Weishi Technology Co., Ltd.
Category: otc | Type: HUMAN OTC DRUG LABEL
Date: 20200507

ACTIVE INGREDIENTS: BENZODODECINIUM BROMIDE 0.376 g/400 mL; METHENAMINE 1.04 g/400 mL
INACTIVE INGREDIENTS: WATER

PURPOSE

Disinfection
Sterilization
No Rinseing

INACTIVE INGREDIENT

water

DOSAGE AND ADMINISTRATION

This product shall be stored in a cool, dry place.

ACTIVE INGREDIENT

Hexamethylenetetramine (0.30%-0.36% (WV); Benzalkonium Bromide(0.18% - 0.22% (WN).

keep out of reach of children

INDICATIONS AND USAGE

This product is applicable for: disinfection of hands and skin of medical staff in various hospital/healthcare departments such as medical surgery, obstetrics and gynecology detection, ICU, CCU, etc., disinfection of hands before and after work for workers in industries requiring clean production such as industries of pharmaceuticals, food, cosmetics, etc.; and disinfection oral mucosa, vaginal mucosa and skin mucosa.

WARNINGS

This product is a disinfectant for external use, and may not be taken orally; it must be kept out of reach of children. This product shall avoid contact with any detergent and antagonist drug. This product cannot be used together with peroxide.